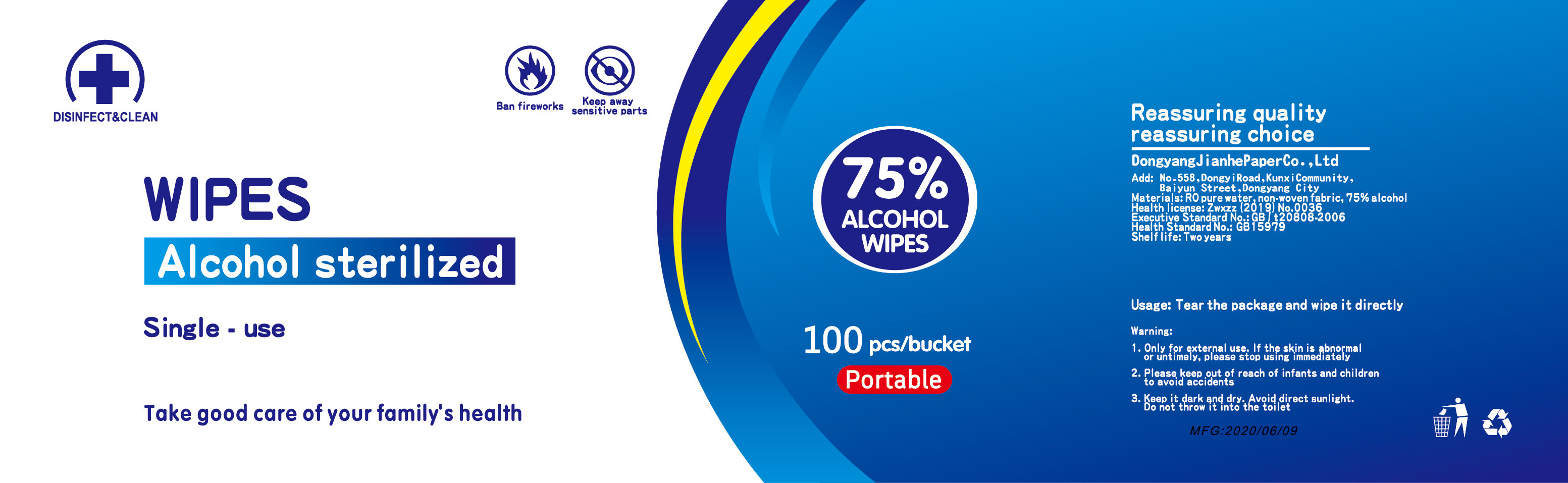 DRUG LABEL: Alcohol sterilized  wipes
NDC: 65872-001 | Form: CLOTH
Manufacturer: Dongyang Jianhe Paper Co., Ltd
Category: otc | Type: HUMAN OTC DRUG LABEL
Date: 20200611

ACTIVE INGREDIENTS: ALCOHOL 150 mL/100 1
INACTIVE INGREDIENTS: POLYESTER (ADIPIC ACID, 1,6-HEXANEDIOL, NEOPENTYL GLYCOL); DIRECT BLACK 19; WATER

DOSAGE AND ADMINISTRATION

Keep it dark and dry. Avoid direct sunlight.

INACTIVE INGREDIENT

water,Polyester，Viscose

INDICATIONS AND USAGE

Tear the package and wipe it directly

ACTIVE INGREDIENT

Alcohol

keep out of reach of children

PURPOSE

Disinfection
Sterilization
No Rinseing

WARNINGS

1. Only for external use. If the skin is abnormal or untimely, please stop using immediately
2. Please keep out of reach of infants and children to avoid acc idents
3. Keep it dark and dry. Avoid direct sunlight.Do not throw it into the toilet